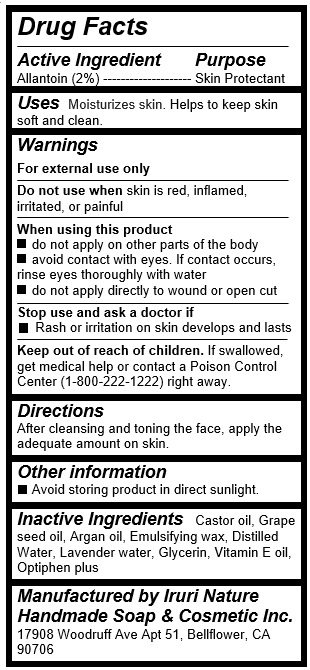 DRUG LABEL: Purple
NDC: 71547-109 | Form: LOTION
Manufacturer: Iruri Nature Handmade Soap & Cosmetic Inc
Category: otc | Type: HUMAN OTC DRUG LABEL
Date: 20170725

ACTIVE INGREDIENTS: ALLANTOIN 0.4 g/20 mL
INACTIVE INGREDIENTS: WATER; GLYCERIN; CASTOR OIL; GRAPE SEED OIL; ARGAN OIL; .ALPHA.-TOCOPHEROL

Purple Lotion (Grape seed & Argan oil)

Active Ingredients

Allantoin (2%)

Purpose

Skin protectant

Uses

Moisturizes skin. Helps to keep skin soft and clean.

Warnings

For external use only

Do not use when skin is red, inflamed, irritated, or painful

When using this product

- do not apply on other parts of the body

- avoid contact with eyes. If contact occurs, rinse eyes thoroughly with water

- do not apply directly to wound or open cut

Stop use and ask a doctor if

- Rash or irritation on skin develops and lasts

Keep out of reach of children

If swallowed, get medical help or contact a Poison Control Center (1-800-222-1222) right away.

Directions

After cleansing and toning the face, apply the adequate amount on skin.

Inactive Ingredients

Castor oil, Grape seed oil, Argan oil, Emulsifying wax, Distilled Water, Lavender water, Glycerin, Vitamin E oil, Optiphen plus